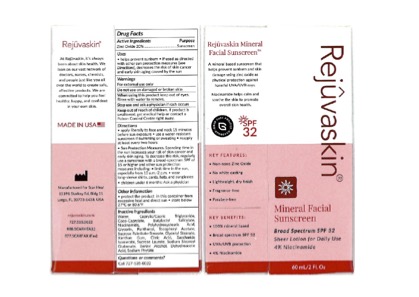 DRUG LABEL: Rejuvaskin Mineral Facial Sunscreen SPF 32 Sheer
NDC: 84375-101 | Form: LOTION
Manufacturer: Atlantic Medical Products, LLC
Category: otc | Type: HUMAN OTC DRUG LABEL
Date: 20260108

ACTIVE INGREDIENTS: ZINC OXIDE 20 g/100 g
INACTIVE INGREDIENTS: DEHYDROACETIC ACID; .ALPHA.-TOCOPHEROL ACETATE; PHYTATE SODIUM; GLYCERIN; SODIUM STEAROYL GLUTAMATE; SUCROSE STEARATE/PALMITATE ESTER (75% MONO ESTER); MEDIUM-CHAIN TRIGLYCERIDES; PANTHENOL; POLYHYDROXYSTEARIC ACID (2300 MW); XANTHAN GUM; NIACINAMIDE; GLYCERYL MONOSTEARATE; COCO-CAPRYLATE; SUCROSE STEARATE; WATER; CITRIC ACID MONOHYDRATE; SACCHARIDE ISOMERATE; SUCROSE LAURATE

ACTIVE INGREDIENT

Zinc Oxide 20%...................Sunscreen

WHEN USING

When using this Product keep out of eyes. Rinse with water to remove.

WARNINGS

For external use only.

STOP USE

Stop use and ask a physician if rash occurs.

Keep out of reach of children. If product is swallowed, get medical help or contact a Poison Control Center right away.

Do not use on damaged or broken skin.

INACTIVE INGREDIENTS

Benzyl Alcohol

Butyloctyl Salicylate

Caprylic/Capric Triglyceride

Citric Acid

Coco-Caprylate

Dehydroacetic Acid

Glycerin

Glyceryl Stearate

Niacinamide

Pathenol

Polyhydroxystearic Acid

Sodium Phytate

Saccharide Isomerate

Sodium Stearoyl Glutamate

Sucrose palmitate-stearate

Sucrose Laurate

Tocopheryl Acetate

Water

Xanthan Gum

PURPOSE

Active Ingredients

Zinc Oxide 20%..............................................Sunscreen

INDICATIONS & USAGE

Uses helps prevent sunburn.

If used as directed with other sun protection measures (see Directions) decreases the risk of skin cancer and early aging caused by the sun.

DOSAGE & ADMINISTRATION

Directions

Apply liberally to face and neck 15 minutes before sun exposure.

Use a water-resistant sunscreen if swimming or sweating.

Reapply at least every two hours.

Sun Protection measures: Spending time in the sun increases your risk of skin cancer and early

skin aging. To decrease this risk, regularly use a sunscreen with broad-spectrum SPF of 15 or

higher and other sun protection measures including

limit time in the sun, especially from 10am - 2pm;

wear long-sleeve shirts, pants, hats, and sunglasses.

Children under 6 months: Ask a physician

PACKAGE LABEL

PRINCIPAL DISPLAY PANEL